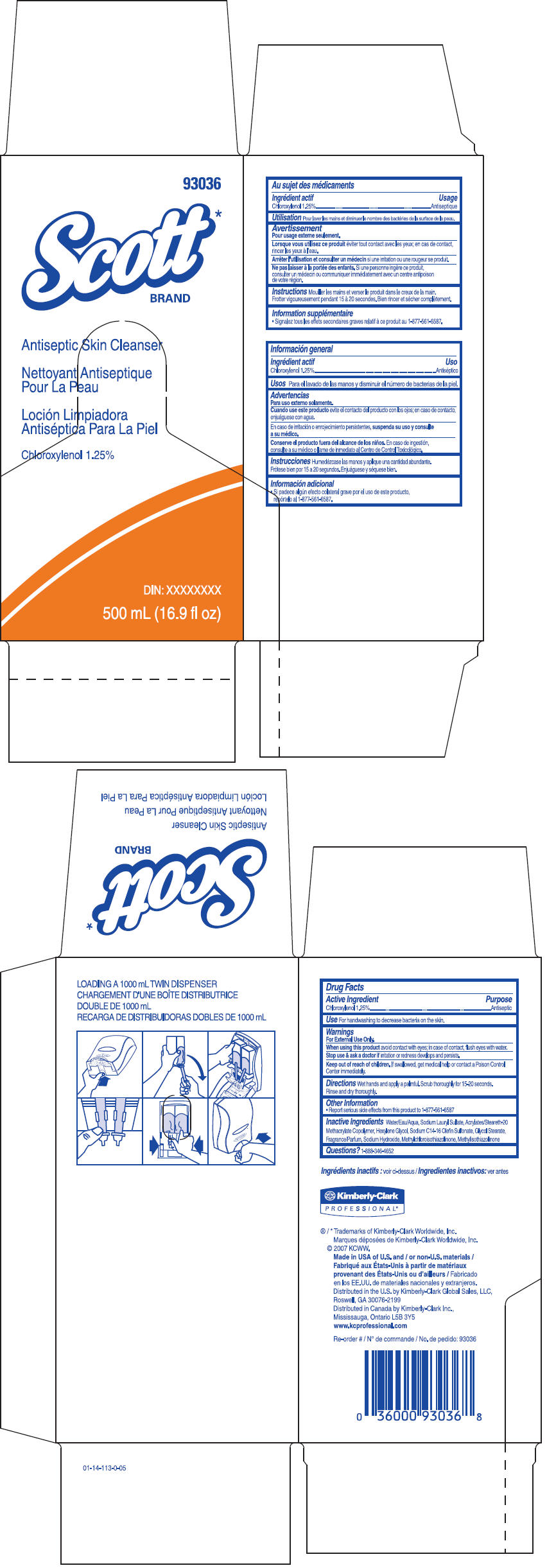 DRUG LABEL: Scott Antiseptic Skin Cleanser
NDC: 55118-245 | Form: SOLUTION
Manufacturer: Kimberly-Clark Corporation
Category: otc | Type: HUMAN OTC DRUG LABEL
Date: 20141007

ACTIVE INGREDIENTS: Chloroxylenol 1.25 g/100 mL
INACTIVE INGREDIENTS: Water; Sodium Laureth-3 Sulfate; Hexylene Glycol; Sodium C14-16 Olefin Sulfonate; Glycol Stearate; Sodium Hydroxide; Methylchloroisothiazolinone; Methylisothiazolinone

Scott Antiseptic Skin Cleanser

Drug Facts

Active Ingredient

Chloroxylenol 1.25%

Purpose

Antiseptic

Use

For handwashing to decrease bacteria on the skin.

Warnings

For External Use Only.

When using this product avoid contact with eyes; in case of contact, flush eyes with water.

Stop use & ask a doctor if irritation or redness develops and persists.

Keep out of reach of children. If swallowed, get mediccal help or contact a Poison Control Center immediately.

Directions

Wet hands and apply a palmful. Scrub thoroughly for 15-20 seconds.

Rinse and dry thoroughly.

Other Information

- Report serious side effects from this product to 1-877-561-6587

Inactive Ingredients

Water, Sodium Lauryl Sulfate, Acrylates/Steareth-20 Methacrylate Copolymer, Hexylene Glycol, Sodium C14-16 Olefin Sulfonate, Glycol Stearate, Fragrance, Sodium Hydroxide, Methylchloroisothiazolinone, Methylisothiazolinone

Questions?

1-888-346-4652

Distributed in the U.S. by Kimberly-Clark Global Sales, LLC,
Roswell,GA 30076-2199

PRINCIPAL DISPLAY PANEL - 500 mL Carton

93036

Scott*
BRAND

Antiseptic Skin Cleanser

Chloroxylenol 1.25%

DIN: XXXXXXXX

500 mL (16.9 fl oz)